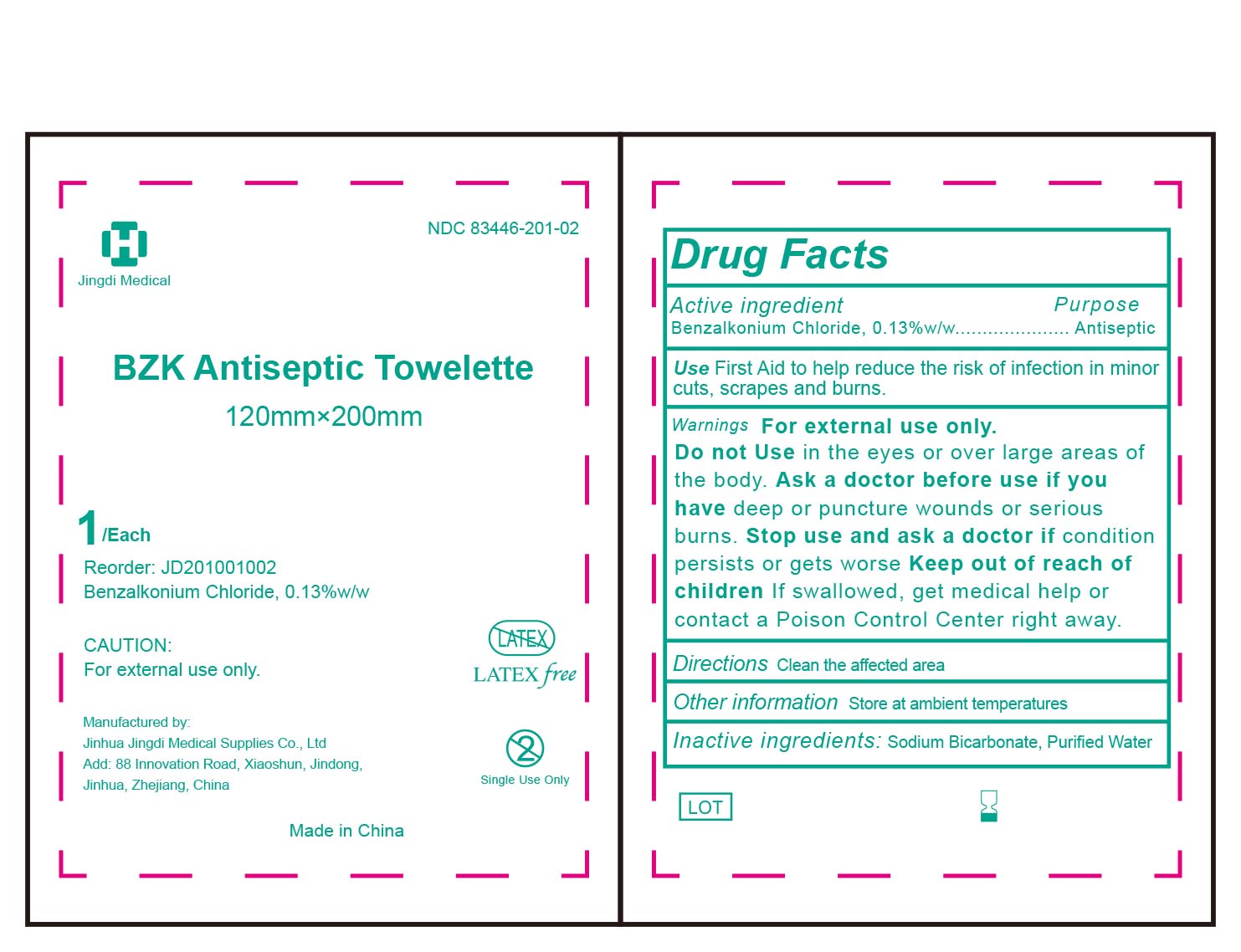 DRUG LABEL: BZK Antiseptic Towelette
NDC: 83446-201 | Form: CLOTH
Manufacturer: JINHUA JINGDI MEDICAL SUPPLIES CO., LTD
Category: otc | Type: HUMAN OTC DRUG LABEL
Date: 20260101

ACTIVE INGREDIENTS: BENZALKONIUM CHLORIDE 1.3 mg/1 g
INACTIVE INGREDIENTS: SODIUM BICARBONATE; WATER

ACTIVE INGREDIENT

Benzalkonium Chloride, 0.13% w/v

DESCRIPTION

First aid to help reduce the risk of infection in minor cuts, scrapes, and burns.

Not made with natural rubber latex.

INACTIVE INGREDIENT

Sodium bicarbonate, purified water

PURPOSE

Antiseptic.

First aid to help reduce the risk of infection in minor cuts, scrapes, and burns.

WARNINGS

For external use only.

KEEP OUT OF REACH OF CHILDREN

If swallowed, get medical help or contact a Poison Control Center right away.

Directions

Clean the affected area.

Do not use in the eyes or over large areas of the body.

Ask a doctor before use if you have deep or puncture wounds or serious burns.

Stop use and ask a doctor if condition persists or gets worse.

DOSAGE AND ADMINISTRATION

Apply topically as needed to cleanse intendend area；
Apply the product to the skin, take the injection or puncture site as the center, slowly rotate from the insideto the outside, and gradually apply the product for two times, the disinfection area should be more than5cmx5cm, and the action time should be 1min.